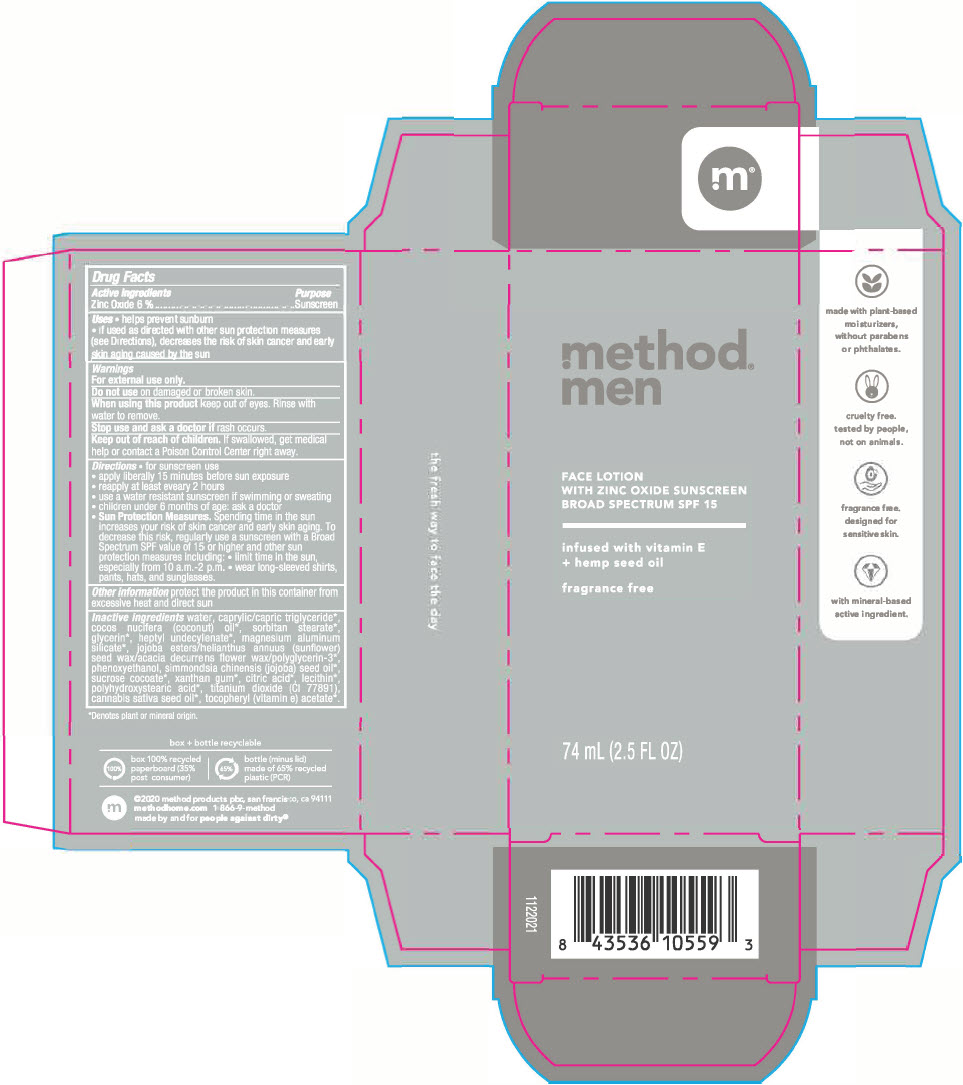 DRUG LABEL: Method Men Face with Zinc Oxide Sunscreen
NDC: 52494-100 | Form: LOTION
Manufacturer: Method Products Inc.
Category: otc | Type: HUMAN OTC DRUG LABEL
Date: 20241212

ACTIVE INGREDIENTS: Zinc Oxide 6 g/100 mL
INACTIVE INGREDIENTS: WATER; MEDIUM-CHAIN TRIGLYCERIDES; COCONUT OIL; SORBITAN MONOSTEARATE; GLYCERIN; HEPTYL UNDECYLENATE; MAGNESIUM ALUMINUM SILICATE; HYDROLYZED JOJOBA ESTERS (ACID FORM); SUNFLOWER OIL; ACACIA DECURRENS FLOWER WAX; POLYGLYCERIN-3; PHENOXYETHANOL; JOJOBA OIL; SUCROSE COCOATE; XANTHAN GUM; ANHYDROUS CITRIC ACID; 1-PALMITOYL-2-LINOLEOYL-SN-GLYCERO-3-PHOSPHOCHOLINE; POLYHYDROXYSTEARIC ACID (2300 MW); TITANIUM DIOXIDE; CANNABIS SATIVA SEED OIL; .ALPHA.-TOCOPHEROL ACETATE; PEG-100 STEARATE

Method® Men Face Lotion with Zinc Oxide Sunscreen

Drug Facts

Active ingredients

Zinc Oxide 6%

Purpose

Sunscreen

Uses

- helps prevent sunburn
- if used as directed with other sun protection measures (see Directions), decreases the risk of skin cancer and early skin aging caused by the sun

Warnings

For external use only.

Do not use on damaged or broken skin.

When using this product keep out of eyes. Rinse with water to remove.

Stop use and ask a doctor if rash occurs.

Keep out of reach of children. If swallowed, get medical help or contact a Poison Control Center right away.

Directions

- for sunscreen use
- apply liberally 15 minutes before sun exposure
- reapply at least eveary 2 hours
- use a water resistant sunscreen if swimming or sweating
- children under 6 months of age: ask a doctor
- Sun Protection Measures. Spending time in the sun increases your risk of skin cancer and early skin aging. To decrease this risk, regularly use a sunscreen with a Broad Spectrum SPF value of 15 or higher and other sun protection measures including:
  - limit time in the sun, especially from 10 a.m. - 2 p.m.
  - wear long-sleeved shirts, pants, hats, and sunglasses.

Other information

protect the product in this container from excessive heat and direct sun

Inactive ingredients

water, caprylic/capric triglyceride [Denotes plant or mineral origin.] , cocos nucifera (coconut) oil, sorbitan stearate, glycerin, heptyl undecylenate, magnesium aluminum silicate, jojoba esters/helianthus annuus (sunflower) seed wax/acacia decurrens flower wax/polyglycerin-3, phenoxyethanol, simmondsia chinensis (jojoba) seed oil, sucrose cocoate, xanthan gum, citric acid, lecithin, polyhydroxystearic acid, titanium dioxide (CI 77891), cannabis sativa seed oil, tocopheryl (vitamin e) acetate.

PRINCIPAL DISPLAY PANEL - 74 mL Bottle Carton

method®
men

FACE LOTION
WITH ZINC OXIDE SUNSCREEN
BROAD SPECTRUM SPF 15

infused with vitamin E
+ hemp seed oil

fragrance free

74 mL (2.5 FL OZ)